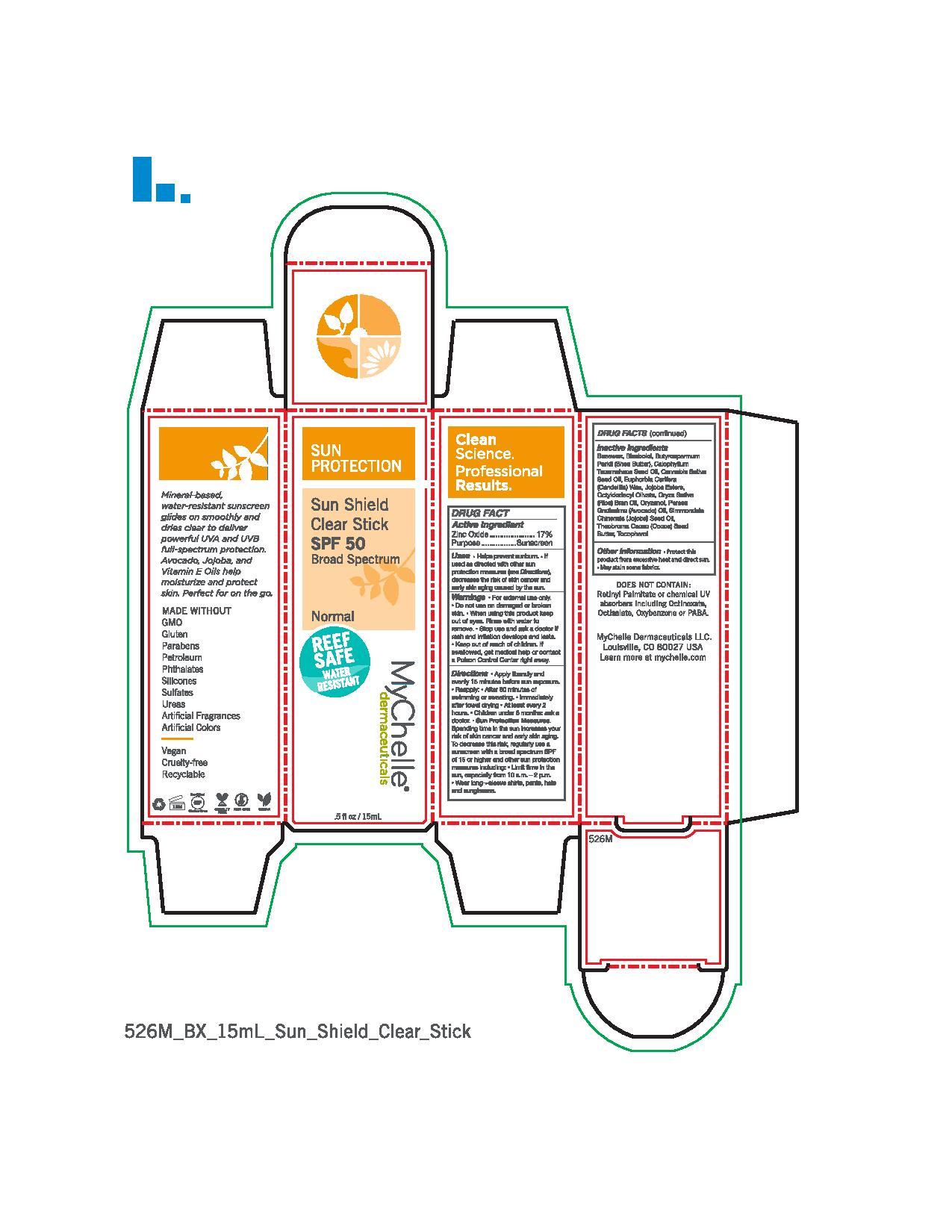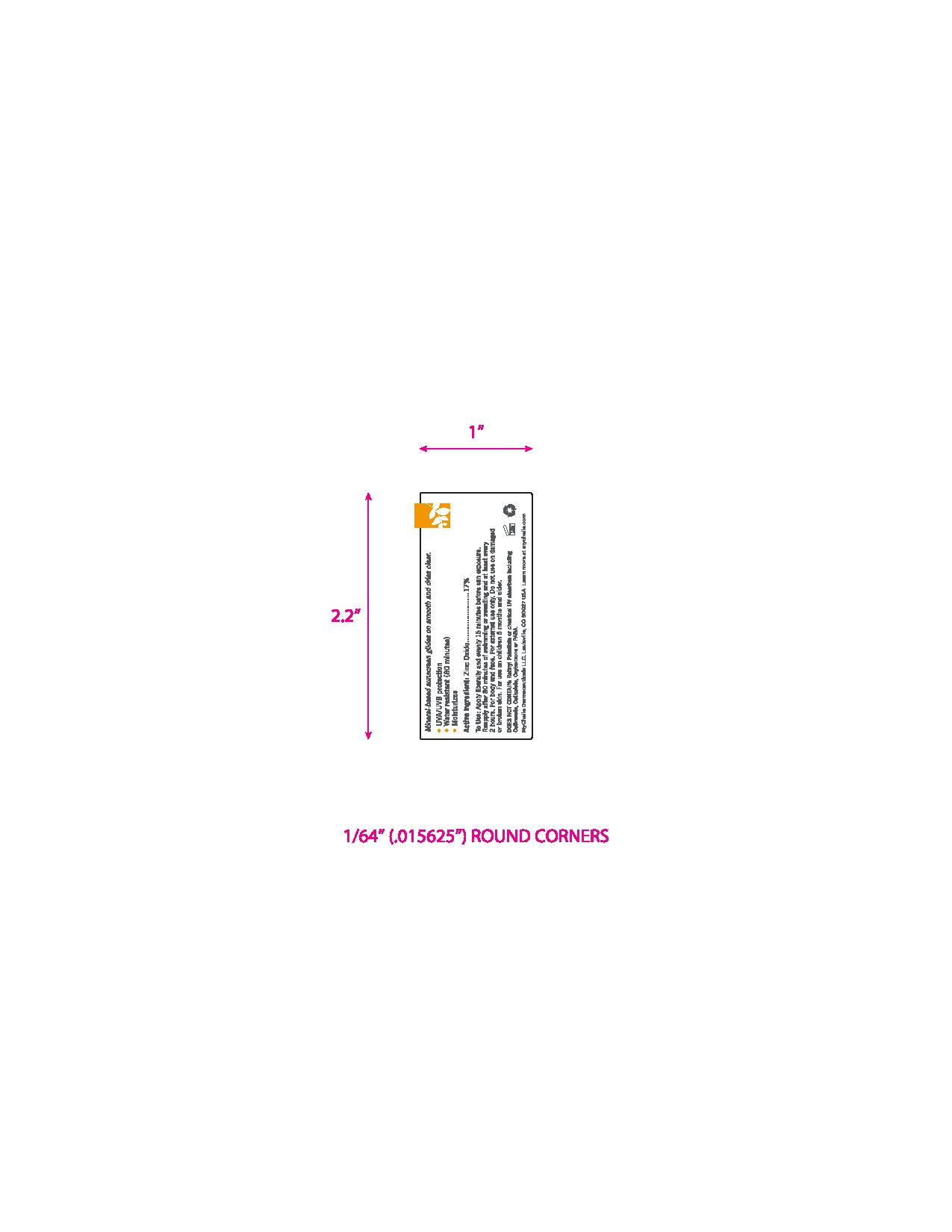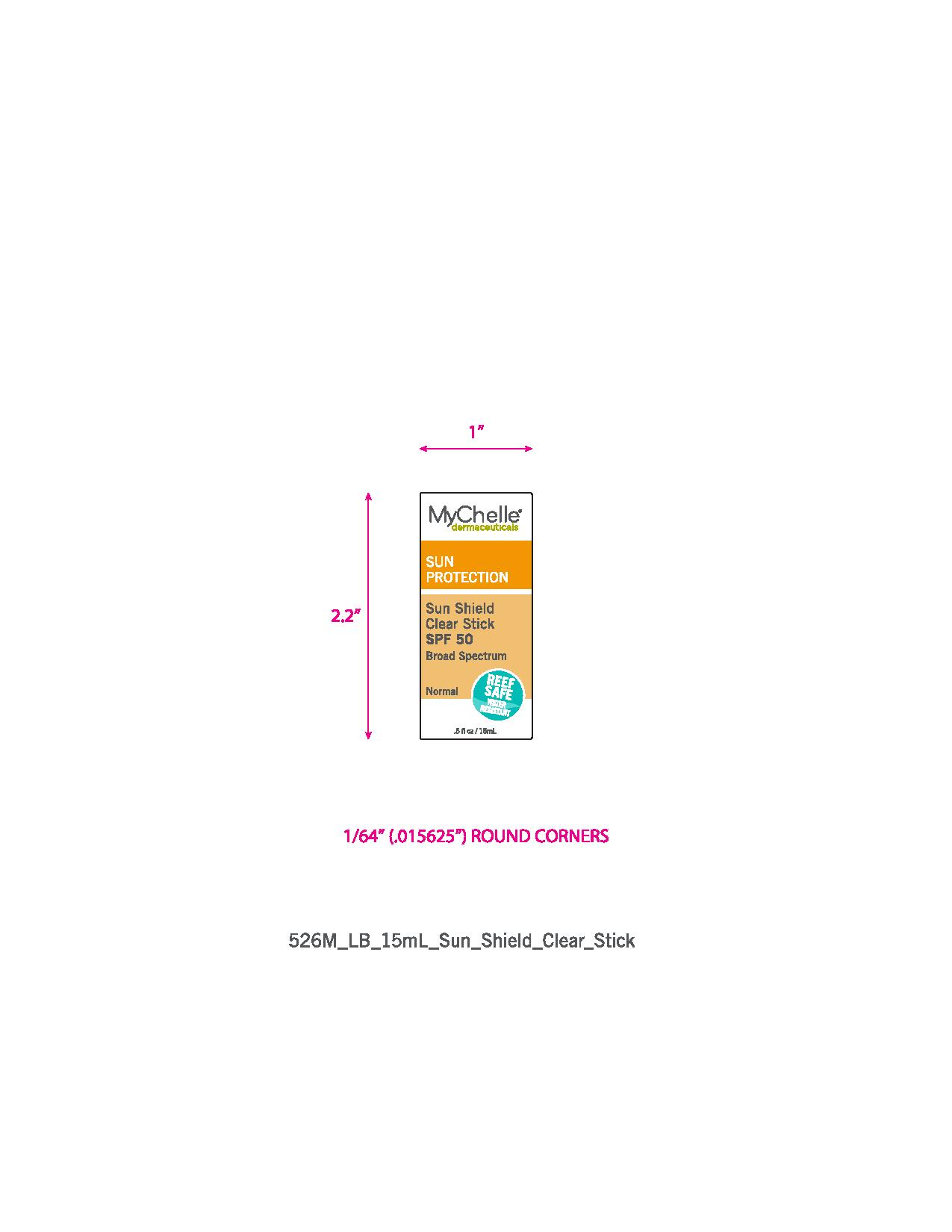 DRUG LABEL: Sun Shield Clear
NDC: 76150-143 | Form: STICK
Manufacturer: Bell International Laboratories, Inc.
Category: otc | Type: HUMAN OTC DRUG LABEL
Date: 20210114

ACTIVE INGREDIENTS: ZINC OXIDE 17 g/100 mL
INACTIVE INGREDIENTS: YELLOW WAX; SHEA BUTTER; CALOPHYLLUM TACAMAHACA SEED OIL; CANNABIS SATIVA SEED OIL; CANDELILLA WAX; HYDROGENATED JOJOBA OIL, RANDOMIZED; RICE BRAN OIL; OCTYLDODECYL OLEATE; LEVOMENOL; GAMMA ORYZANOL; AVOCADO OIL; JOJOBA OIL; COCOA BUTTER; TOCOPHEROL

Mychelle Dermaceuticals Sun Shield Clear SPF 50 Mineral Stick

Active Ingredient

Zinc Oxide........17%

Purpose

Sunscreen

Uses

Helps prevent sunburn.

If used as directed with other sun protection measures (see Directions), decreases the risk of skin cancer and early skin aging caused by the sun.

Warnings

- For external use only.
- Do not use on damaged or broken skin.
- When using this product keep out of eyes. Rinse with water to remove.
- Stop use and ask a doctor if rash and irritation develops and lasts.

Keep out of reach of children. If swallowed, get medical help or contact a Poison Control Center right away.

Directions

- Apply liberally and evenly 15 minutes before sun exposure.
- Reapply:
  - After 80 minutes of swimming or sweating.
  - Immediately after towel drying
  - At least every 2 hours.
  - Children under 6 months: ask a doctor.
  - Sun Protection Measures. Spending time in the sun increases your risk of skin cancer and early skin aging. To decrease this risk, regularly use a sunscreen with a borad spectrum SPF of 15 or higher and other sun protection measures including:
  - Limit time in the sun, especially from 10a.m. - 2 p.m.
  - Wear long-sleeved shirts, pants, hats and sunglasses.

Inactive Ingredients

Beeswax, Bisabolol, Butyrospermum Parkii (Shea Butter), Calophyllum Tacamahaca Seed Oil, Cannabis Sativa Seed Oil, Euphorbia Cerifera (Candelilla) Wax, Jojoba Esters, Octyldodecyl Olivate, Oryza Sativa (Rice) Bran Oil, Oryzanol, Persea Gratissima (Avocado) Oil, Simmondsia Chinensis (Jojoba) Seed Oil, Theobroma Cacao (Cocoa) Seed Butter, Tocopherol.

Other Information

Protect this product from excessive heat and direct sun.

May stain some fabrics.